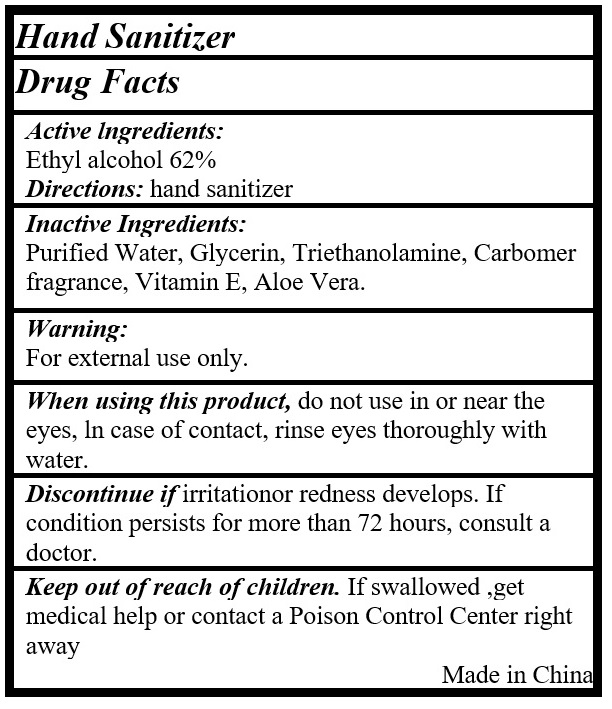 DRUG LABEL: Hand sanitizer
NDC: 73357-627 | Form: GEL
Manufacturer: Hangzhou Lanqueen Cosmetics Co., Ltd.
Category: otc | Type: HUMAN OTC DRUG LABEL
Date: 20200410

ACTIVE INGREDIENTS: ALCOHOL 62 mL/100 mL
INACTIVE INGREDIENTS: WATER; GLYCERIN; TROLAMINE; CARBOMER HOMOPOLYMER, UNSPECIFIED TYPE; .ALPHA.-TOCOPHEROL; ALOE VERA LEAF

Hand Sanitizer

Active Ingredients:

Ethyl alcohol 62%

PURPOSE

Antiseptic

Uses:

Hand sanitizer

Warning:

For external use only.

When using this product, do not use in or near the eyes, ln case of contact, rinse eyes thoroughly with water.

Discontinue if irritation or redness develops. If condition persists for more than 72 hours, consult a doctor.

Keep out of reach of children. If swallowed, get medical help or contact a Poison Control Center right away

Directions:

Place enough product in palm to cover hands and rub hands together briskly until dry.

Inactive Ingredients:

Purified Water, Glycerin, Triethanolamine, Carbomer fragrance, Vitamin E, Aloe Vera.

Made in China